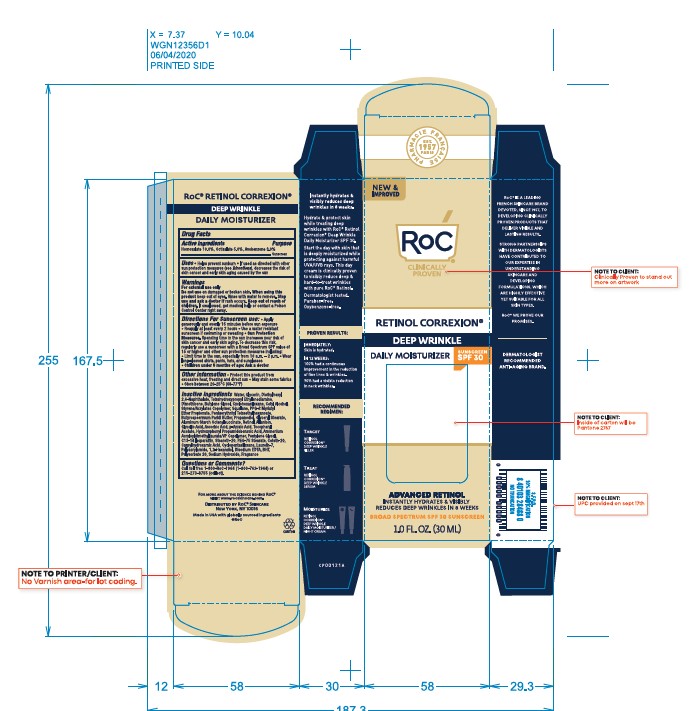 DRUG LABEL: ROC RETINOL CORREXION WRINKLE CORRECT DAILY MOISTURIZER SPF 30
NDC: 73496-004 | Form: LOTION
Manufacturer: Roc Skincare
Category: otc | Type: HUMAN OTC DRUG LABEL
Date: 20241127

ACTIVE INGREDIENTS: HOMOSALATE 10 mg/100 mL; OCTISALATE 5 mg/100 mL; AVOBENZONE 3 mg/100 mL
INACTIVE INGREDIENTS: CYCLOMETHICONE 5; BUTYLATED HYDROXYTOLUENE; SODIUM HYDROXIDE; EDETOL; ALPHA-TOCOPHEROL ACETATE; CETETH-20; LAURETH-7; WATER; DIETHYLHEXYL 2,6-NAPHTHALATE; SHEA BUTTER; SQUALANE; GLYCERYL STEARATE SE; ALUMINUM STARCH OCTENYLSUCCINATE; GLYCOLIC ACID; ASCORBYL PALMITATE; CAPRYLHYDROXAMIC ACID; CETYL ALCOHOL; ALLANTOIN; PEG-8 LAURATE; PEG-75 STEARATE; PPG-2 MYRISTYL ETHER PROPIONATE; PENTAERYTHRITYL TETRAETHYLHEXANOATE; PROPANEDIOL; RETINOL; P-ANISIC ACID; PENTYLENE GLYCOL; C13-14 ISOPARAFFIN; AMMONIUM ACRYLOYLDIMETHYLTAURATE/VP COPOLYMER; CYCLOMETHICONE 6; BUTYLENE GLYCOL; STEARETH-20; POLYSORBATE 20; ASCORBIC ACID; EDETATE DISODIUM; HYDROXYPHENYL PROPAMIDOBENZOIC ACID; 1,2-HEXANEDIOL; GLYCERIN; DIMETHICONE

ROC RETINOL CORREXION WRINKLE CORRECT DAILY MOISTURIZER SPF 30

ACTIVE INGREDIENT

Avobenzone 3.0%, Homosalate 10.0%, Octisalate 5.0 %.......Sunscreen

Uses

- Helps prevent sunburn
- If used as directed with other sun protection measures (see Directions), decreases the risk of skin cancer and early skin aging caused by the sun

Warnings

For external use only

Do not use on damaged or broken skin. When using this product keep out of eyes. Rinse with water to remove. Stop use and ask a doctor if rash occurs. Keep out of reach of children. If swallowed, get medical help or contact a Poison Control Center right away.

Keep out of reach of children.

Directions for Sunscreen use

- Apply generously and evenly 15 minutes before sun exposure
- Reapply at least every 2 hours
- Use a water resistant sunscreen if swimming or sweating
- Sun Protection Measures. Spending time in the sun increases your risk of skin cancer and early skin aging. To decrease this risk, regularly use a sunscreen with a Broad Spectrum SPF value of 15 or higher and other sun protection measures including:
- Limit time in the sun, especially from 10 a.m. - 2 p.m.
- Wear long-sleeved shirts, pants, hats, and sunglasses
- Children under 6 months of age: Ask a doctor

Other information

- Protect this product from excessive heat, freezing and direct sun
- May stain some fabrics
- Store between 20-25 °C (68-77 °F)

INACTIVE INGREDIENT

Water, Glycerin, Diethylhexyl 2,6-Naphthalate, Dimethicone, Tetrahydroxypropyl Ethylenediamine, Butylene Glycol, Cyclohexasiloxane, Cetyl Alcohol, Butyrospermum Parkii (Shea) Butter, PPG-2 Myristyl Ether Propionate, Pentaerythrityl Tetraethylhexanoate, Squalane, Propanediol, Styrene/Acrylates Copolymer, Glyceryl Stearate, Aluminum Starch Octenylsuccinate, Retinol, Glycolic Acid, Tocopheryl Acetate, Ascorbyl Palmitate, Allantoin, p-Anisic Acid, Pentylene Glycol, Ceteth-20, Steareth-20, Polyacrylamide, PEG-8 Laurate, Laureth-7, C13-14 Isoparaffin, Ammonium Acryloyldimethyltaurate/VP Copolymer, PEG-75 Stearate, Cyclopentasiloxane, Polysorbate 20, Ascorbic Acid, Hydroxyphenyl Propamidobenzoic Acid, Caprylhydroxamic Acid, 1,2-Hexanediol, BHT, Disodium EDTA, Sodium Hydroxide, Fragrance.

Questions or Comments?

Call toll free 1-800-RoC-1964 (1-800-762-1964) or 215-273-8755 (collect).

INDICATIONS AND USAGE

- Apply generously and evenly 15 minutes before sun exposure
- Reapply at least every 2 hours
- Use a water resistant sunscreen if swimming or sweating
- Sun Protection Measures. Spending time in the sun increases your risk of skin cancer and early skin aging. To decrease this risk, regularly use a sunscreen with a Broad Spectrum SPF value of 15 or higher and other sun protection measures including:
- Limit time in the sun, especially from 10 a.m. - 2 p.m.
- Wear long-sleeved shirts, pants, hats, and sunglasses
- Children under 6 months of age: Ask a doctor